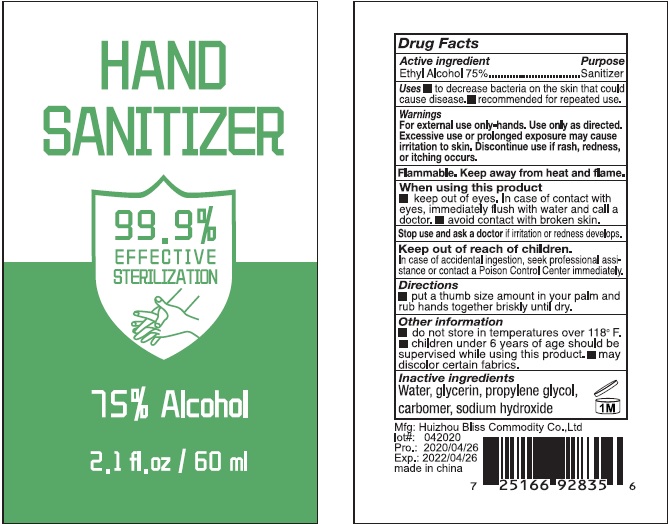 DRUG LABEL: Hand Sanitizer
NDC: 74274-008 | Form: SOLUTION
Manufacturer: Huizhou Bliss Commodity Co., Ltd
Category: otc | Type: HUMAN OTC DRUG LABEL
Date: 20200418

ACTIVE INGREDIENTS: ALCOHOL 75 mL/100 mL
INACTIVE INGREDIENTS: WATER; CARBOMER INTERPOLYMER TYPE A (ALLYL SUCROSE CROSSLINKED); GLYCERIN; PROPYLENE GLYCOL; SODIUM HYDROXIDE

Active ingredient

Ethyl Alcohol 75%

Purpose

Sanitizer

Use

- to decrease bacteria on the skin that could cause disease.
- recommended for repeated use.

KEEP OUT OF REACH OF CHILDREN

In case of accidental ingestion, seek professional assistance or contact a Poison Control Center immediately.

warnings:

Flamable, keep away from heat and flame

For external use onl-hands. Use only as directed. Excessive use or prolonged exposure may cause irritation to skin. Discontinue use if rash, redness or itching occurs.

When using this product

- keep out of eyes, in case of contact with eyes, immediately flush with water and call a doctor.
- avoid contact with broken skin

Stop use and ask a doctor if Irritation and redness develops

Directions

put a thumb size amount in your palm and rub hands together briskly until dry.

Other Information

- do not store in temperatures over 118℉
- children under 6 years of age should be supervised while using this product
- may discolor certain fabrics

Inactive ingredients

Water, glycerin, propyene glycol, carbomer, sodium hydroxide